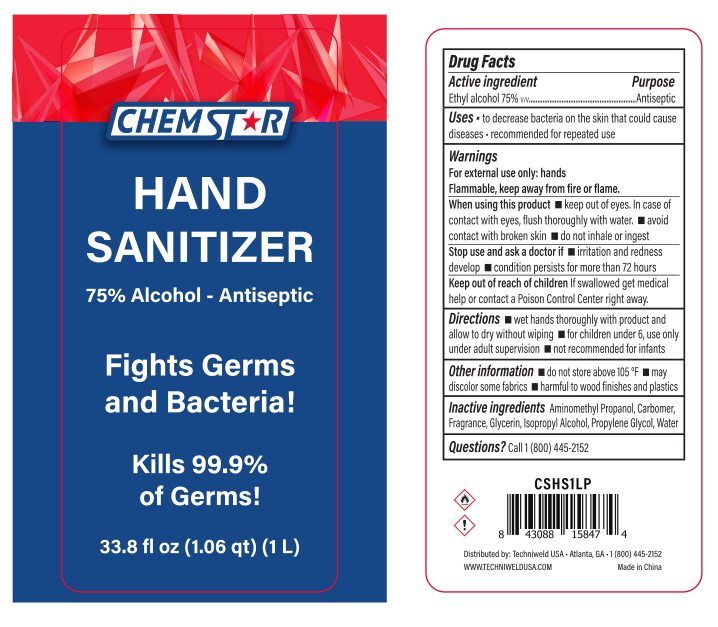 DRUG LABEL: CHEMSTAR hand sanitizer 1L
NDC: 79690-002 | Form: LIQUID
Manufacturer: Techniweld USA
Category: otc | Type: HUMAN OTC DRUG LABEL
Date: 20200724

ACTIVE INGREDIENTS: ALCOHOL 75 mL/100 mL
INACTIVE INGREDIENTS: PROPYLENE GLYCOL 0.01 mL/100 mL; CARBOMER 940 0.35 mL/100 mL; AMINOMETHYLPROPANOL 0.11 mL/100 mL; WATER 24.42 mL/100 mL; GLYCERIN 0.01 mL/100 mL

CHEMSTAR hand sanitizer 1L

Active Ingredient

Active Ingredient Purpose

Ethyl Alcohol 75%（V/V） Antiseptic

keep out of reach of children

If swallowed,get medical help or contact a Poison Control Center right away.

DOSAGE AND ADMINISTRATION

Recommended for repeated use.

use anywhere without water.

Warning

For external use only:hands

Flammable,keep away from fire or flame.

WARNINGS AND PRECAUTIONS

For external use only.

Flammable, keep away from heat and flame.

STOP USE

Discontinue if skin becomes irritated and ask a doctor .

Keep out of reach of children. In case of accidental ingestion, seek professional assistance or contact a poson control center immediately.

Inactive ingredients

Water,Aminomethyl propanol,Carbomer,Fragrance,Glycerin,Isopropyl Alcohol,Propylene Glycol.

Directions

wet hands thoroughly with product and allow to dry without wiping

for children under 6,use only under adult supervision

not recommended for infants.

When using this product

keep out of eyes. In case of contact with eyes, flush thoroughly with water.

Do not inhale or ingest.

Avoid contact with broken skin.

Other information

Do not store above 105F.

May discolor some fabrics.

Harmful to wood finishes and plastics.

When using this product

Keep out of eyes.In case of contact with eyes,flash thoroughly with water.Avoid contact with broken skin.Do not inhale or ingest.

Other information

Do not store above 105℉

may discolor some fabrics

harmful to wood finishes and plastics.

Use

to decrease bacteria on the skin that could cause diseases.recommended for repeated use.